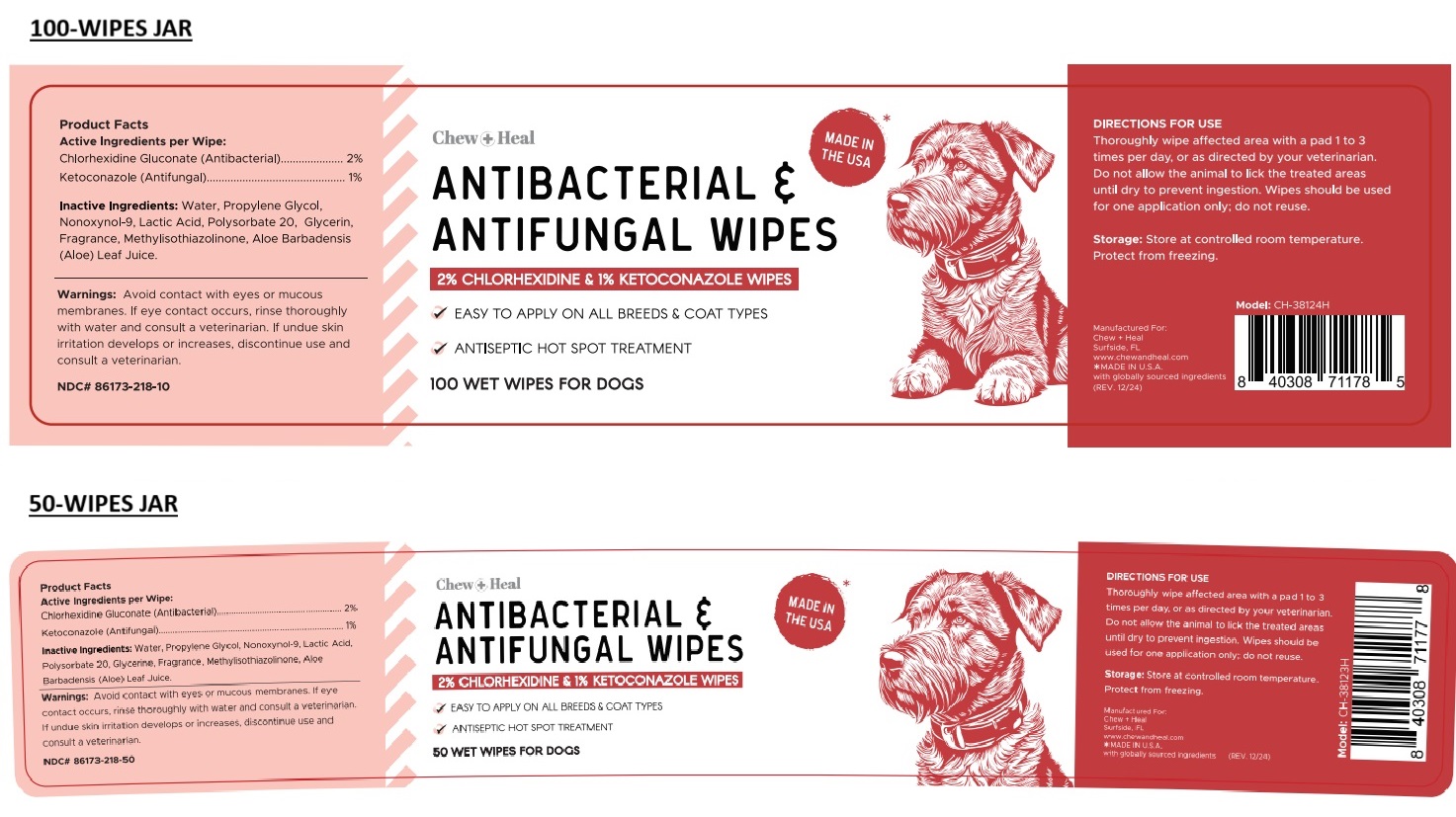 DRUG LABEL: Chew Plus Heal ANTIBACTERIAL AND ANTIFUNGAL WIPES
NDC: 86173-218 | Form: CLOTH
Manufacturer: Click Industries LLC
Category: animal | Type: OTC ANIMAL DRUG LABEL
Date: 20241212

ACTIVE INGREDIENTS: CHLORHEXIDINE GLUCONATE 2 g/100 mL; KETOCONAZOLE 1 g/100 mL
INACTIVE INGREDIENTS: WATER; PROPYLENE GLYCOL; NONOXYNOL-9; LACTIC ACID, UNSPECIFIED FORM; POLYSORBATE 20; GLYCERIN; METHYLISOTHIAZOLINONE; ALOE VERA LEAF

Chew+Heal ANTIBACTERIAL & ANTIFUNGAL WIPES

Active Ingredients per Wipe:

Chlorhexidine Gluconate (Antibacterial)...... 2%
Ketoconazole (Antifungal)...... 1%

Inactive Ingredients:

Water, Propylene Glycol, Nonoxynol-9, Lactic Acid, Polysorbate 20, Glycerin, Fragrance, Methylisothiazolinone, Aloe Barbadensis (Aloe) Leaf Juice.

Warnings:

Avoid contact with eyes or mucous membranes. If eye contact occurs, rinse thoroughly with water and consult a veterinarian. If undue skin irritation develops or increases, discontinue use and consult a veterinarian.

DIRECTIONS FOR USE

Thoroughly wipe affected area with a pad 1 to 3 times per day, or as directed by your veterinarian. Do not allow the animal to lick the treated areas until dry to prevent ingestion. Wipes should be used for one application only; do not reuse.

Storage:

Store at controlled room temperature. Protect from freezing.

MADE IN THE USA*

√ EASY TO APPLY ON ALL BREEDS & COAT TYPES

√ ANTISEPTIC HOT SPOT TREATMENT

WET WIPES FOR DOGS

Manufactured For:
Chew + Heal
Surfside, FL
www.chewandheal.com
*MADE IN U.S.A.
with globally sourced ingredients
(REV. 12/24)